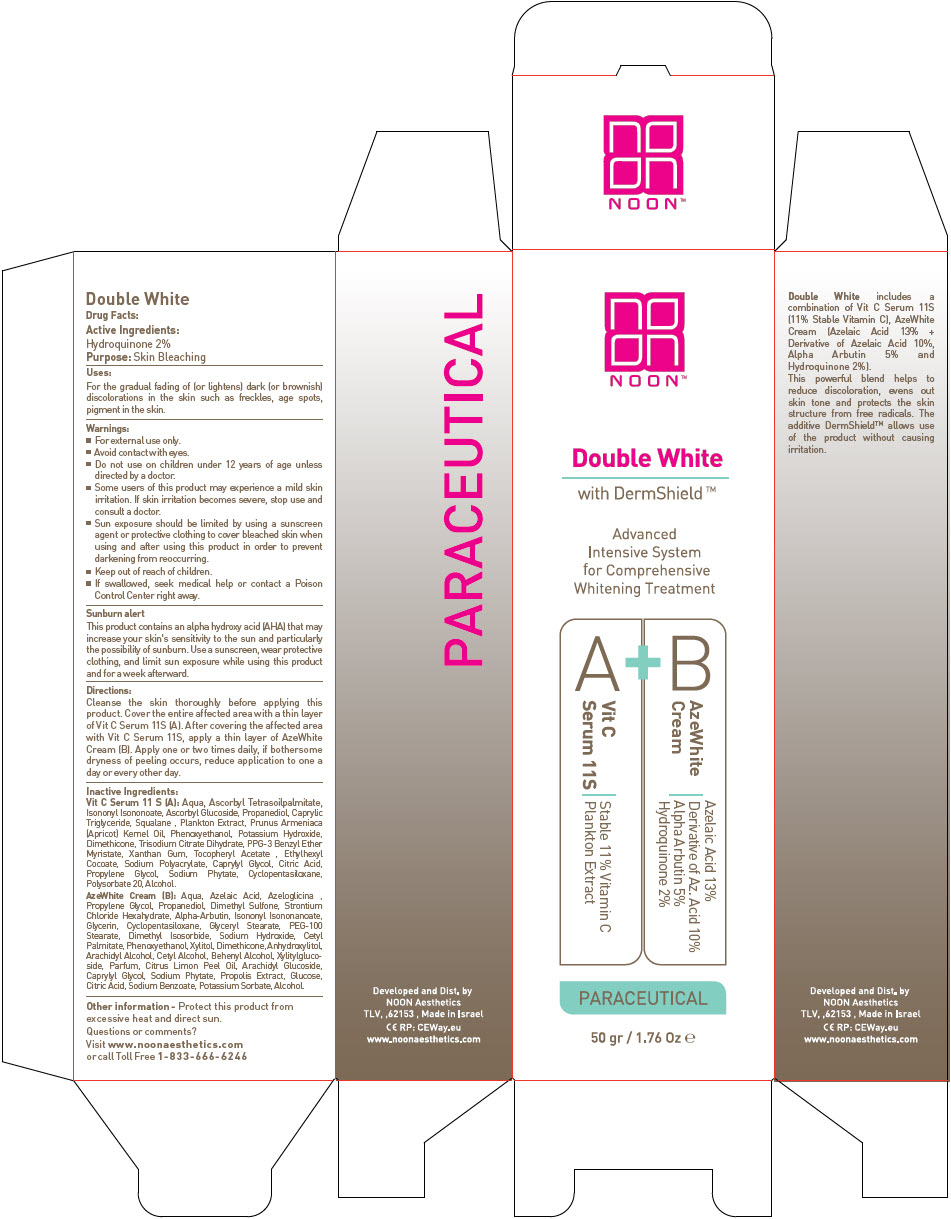 DRUG LABEL: Double White
NDC: 78863-1050 | Form: KIT | Route: TOPICAL
Manufacturer: Noon Aesthetics M.R. Ltd
Category: otc | Type: HUMAN OTC DRUG LABEL
Date: 20210412

ACTIVE INGREDIENTS: Hydroquinone 0.5 g/25 g
INACTIVE INGREDIENTS: Propanediol; Propylene Glycol; Azelaic Acid; Water; Sodium Hydroxide; Alcohol; Alpha-Arbutin; Dimethyl Sulfone; Strontium Chloride Hexahydrate; Glycerin; Arachidyl Alcohol; Arachidyl Glucoside; Anhydrous Dextrose; Glyceryl Monostearate; PEG-100 Stearate; Cetyl Palmitate; Dimethyl Isosorbide; Cetyl Alcohol; Isononyl Isononanoate; Phenoxyethanol; Caprylyl Glycol; Docosanol; Cyclomethicone 5; Dimethicone; Xylitylglucoside; Anhydroxylitol; Xylitol; Propolis Wax; Citric Acid Monohydrate; Sodium Benzoate; Potassium Sorbate; Pummelo; Lemon Oil; Phytate Sodium; Potassium Azeloyl Diglycinate

Double White

Drug Facts:

Active Ingredients

Hydroquinone 2%

Purpose

Skin Bleaching

Uses

For the gradual fading of (or lightens) dark (or brownish) discolorations in the skin such as freckles, age spots, pigment in the skin.

Warnings

- For external use only.
- Avoid contact with eyes.
- Do not use on children under 12 years of age unless directed by a doctor.
- Some users of this product may experience a mild skin irritation. If skin irritation becomes severe, stop use and consult a doctor.
- Sun exposure should be limited by using a sunscreen agent or protective clothing to cover bleached skin when using and after using this product in order to prevent darkening from reoccurring.

- Keep out of reach of children.
- If swallowed, seek medical help or contact a Poison Control Center right away.

Sunburn alert

This product contains an alpha hydroxy acid (AHA) that may increase your skin's sensitivity to the sun and particularly the possibility of sunburn. Use a sunscreen, wear protective clothing, and limit sun exposure while using this product and for a week afterward.

Directions

Cleanse the skin thoroughly before applying this product. Cover the entire affected area with a thin layer of Vit C Serum 11S (A). After covering the affected area with Vit C Serum 11S, apply a thin layer of AzeWhite Cream (B). Apply one or two times daily, if bothersome dryness of peeling occurs, reduce application to one a day or every other day.

Inactive Ingredients

Vit C Serum 11 S (A)

Aqua, Ascorbyl Tetrasoilpalmitate, Isononyl Isononoate, Ascorbyl Glucoside, Propanediol, Caprylic Triglyceride, Squalane , Plankton Extract, Prunus Armeniaca (Apricot) Kernel Oil, Phenoxyethanol, Potassium Hydroxide, Dimethicone, Trisodium Citrate Dihydrate, PPG-3 Benzyl Ether Myristate, Xanthan Gum, Tocopheryl Acetate , Ethylhexyl Cocoate, Sodium Polyacrylate, Caprylyl Glycol, Citric Acid, Propylene Glycol, Sodium Phytate, Cyclopentasiloxane, Polysorbate 20, Alcohol.

AzeWhite Cream (B)

Aqua, Azelaic Acid, Azeloglicina , Propylene Glycol, Propanediol, Dimethyl Sulfone, Strontium Chloride Hexahydrate, Alpha-Arbutin, Isononyl Isononanoate, Glycerin, Cyclopentasiloxane, Glyceryl Stearate, PEG-100 Stearate, Dimethyl Isosorbide, Sodium Hydroxide, Cetyl Palmitate, Phenoxyethanol, Xylitol, Dimethicone, Anhydroxylitol, Arachidyl Alcohol, Cetyl Alcohol, Behenyl Alcohol, Xylitylglucoside, Parfum, Citrus Limon Peel Oil, Arachidyl Glucoside, Caprylyl Glycol, Sodium Phytate, Propolis Extract, Glucose, Citric Acid, Sodium Benzoate, Potassium Sorbate, Alcohol.

Other information

Protect this product from excessive heat and direct sun.

Questions or comments?

Visit www. noonaesthetics. com
or call Toll Free 1-833-666-6246

Developed and Dist. by
NOON Aesthetics
TLV,,62153 , Made in Israel

PRINCIPAL DISPLAY PANEL - 50 gr Kit Carton

NOON™

Double White

with DermShield ™

Advanced
Intensive System
for Comprehensive
Whitening Treatment

A
Vit C
Serum 11S
Stable 11% Vitamin C
Plankton Extract

+

B
AzeWhite
Cream
Azelaic Acid 13%
Derivative of Az. Acid 10%
Alpha Arbutin 5%
Hydroquinone 2%

PARACEUTICAL

50 gr / 1.76 Oz e